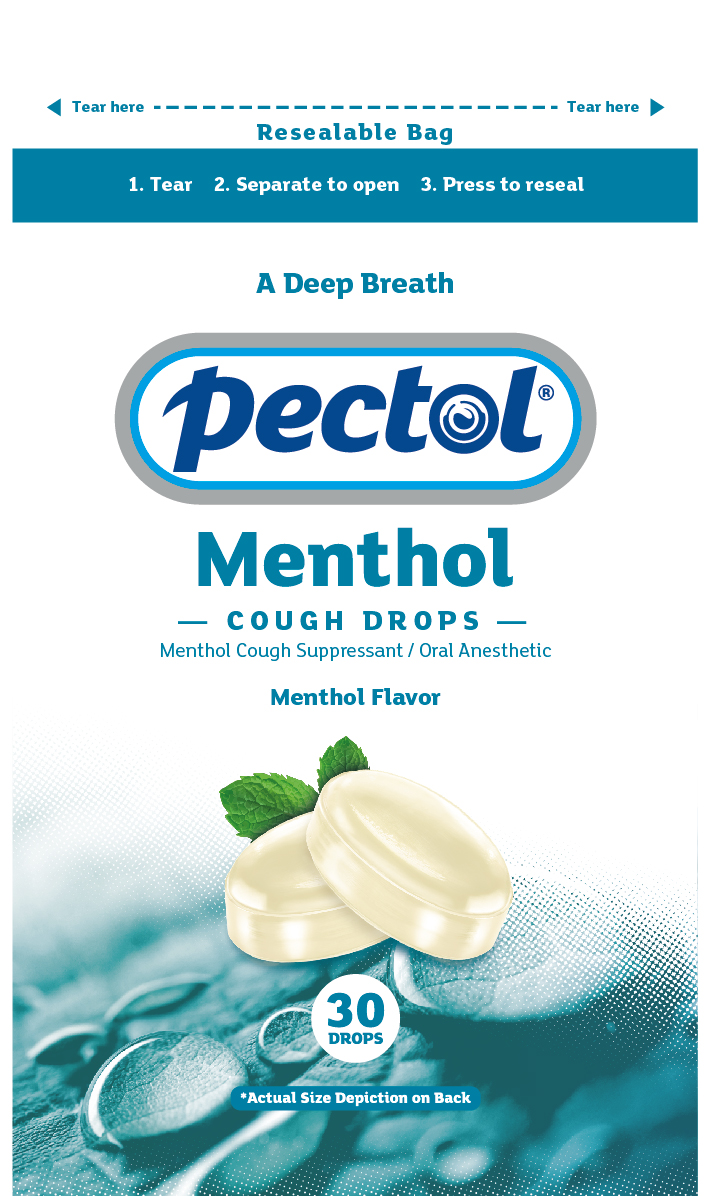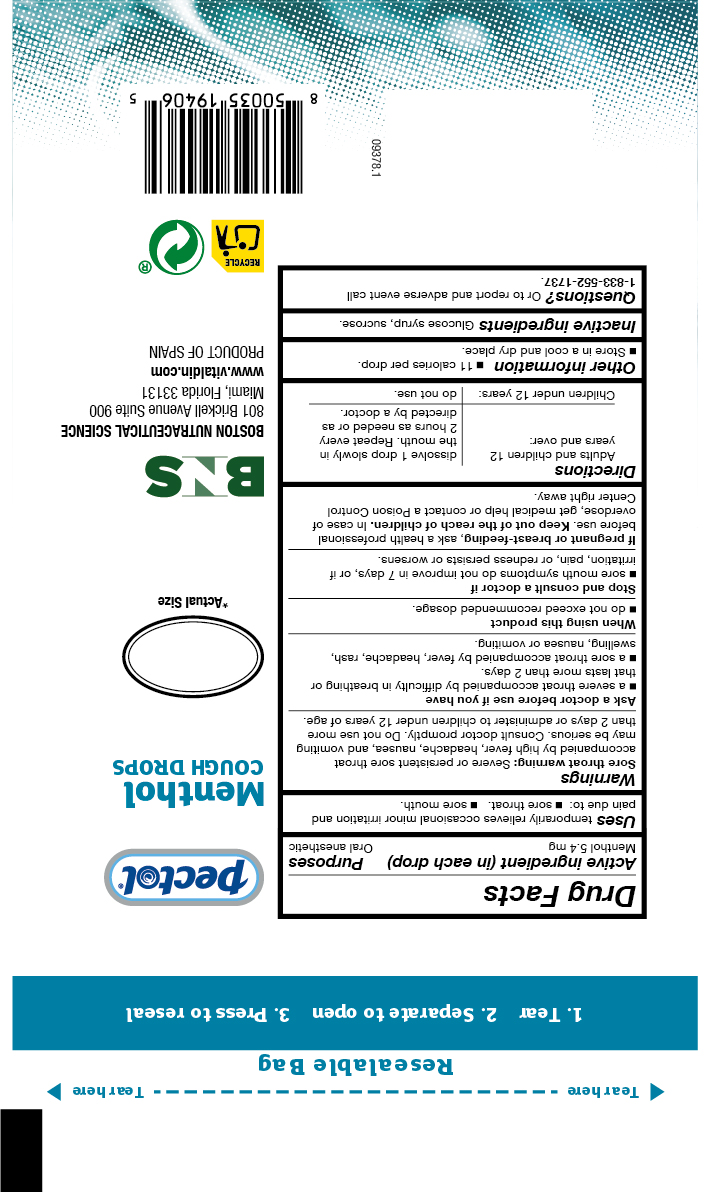 DRUG LABEL: Menthol Cough Drops
NDC: 72628-118 | Form: PASTILLE
Manufacturer: BOSTON NUTRACEUTICAL PRODUCTION, S.L
Category: otc | Type: HUMAN OTC DRUG LABEL
Date: 20241029

ACTIVE INGREDIENTS: MENTHOL 5.4 mg/1 1
INACTIVE INGREDIENTS: CORN SYRUP; SUCROSE

PECTOL
MENTHOL COUGH DROPS
Menthol Cough Suppressant/ Oral Anesthetic
Menthol Flavor

Active Ingredient in each drop Purposes

Menthol 5.4 mg

Cough Suppressant

Oral Anesthetic

Purposes

Temporarily relieves ocassional minor irritation and pain due to:

- sore throat
- sore mouth

Purposes

Temporarily relieves ocassional minor irritation and pain due to:

- sore throat
- sore mouth

Warnings

Sore throat warning: severe or persistant sore throat accompanied by high fever headache, nausea and vomiting maybe serious Consult a doctor promptly. Do not use more than 2 days or administer to children under 12 years old.

Ask a doctor before use if you have:

- a severe throat accompanied by difficulty in breathing or that lasts more than 2 days
- a sore throat accompanied by fever, headache, rash, swelling, nausea and vomiting

Stop use and consult doctor if

- sore mouth symptons does not improve in 7 days or if,
- irritation, pain or redness persists or worsens

PREGNANCY OR BREAST FEEDING

If pregnant or breast-feeding, ask a health professional before use.

Keep out of the reach of children.

OVERDOSAGE

In case of accidental overdose, get medical help or contact a Poison Control Center right away.

Directions

- Adults and children 12 years and over: dissolve 1 drop slowly in mouth. Repeat every two hours as needed or as directed by a doctor.
- Children under 12 years do not use

Other information

- Store in a cool and dry place
- 11 calories per drop

INACTIVE INGREDIENT

glucose, syrup, sucrose

Questions or to report an adverse event call:

1 833 5521737